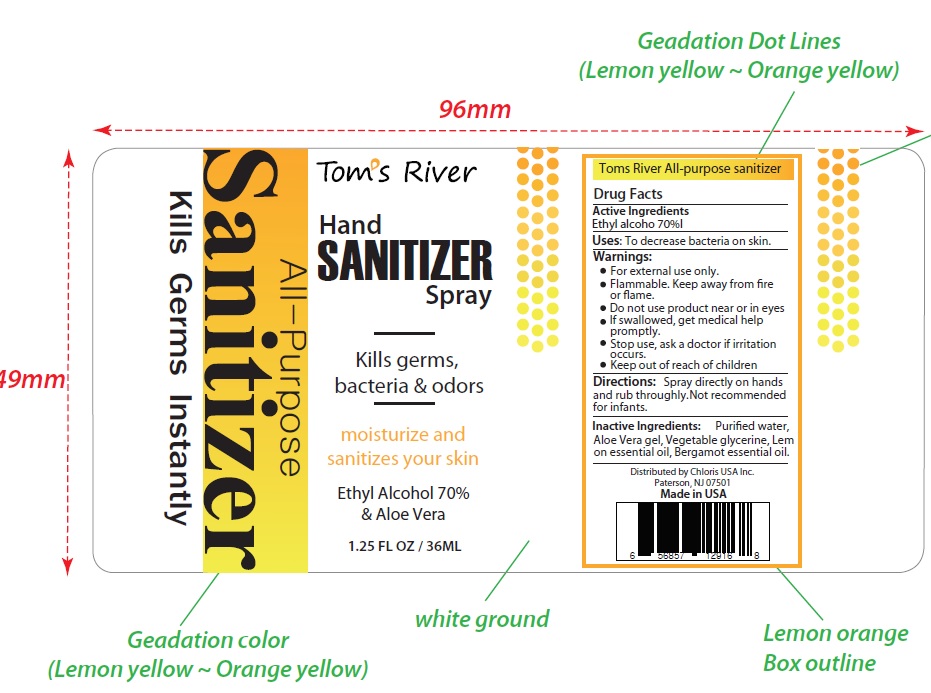 DRUG LABEL: Toms River
NDC: 77728-001 | Form: LIQUID
Manufacturer: Chloris USA Inc
Category: otc | Type: HUMAN OTC DRUG LABEL
Date: 20200508

ACTIVE INGREDIENTS: ALCOHOL 70 mL/100 mL
INACTIVE INGREDIENTS: LEMON OIL, DISTILLED; GLYCERIN; WATER; BERGAMOT OIL; ALOE VERA LEAF

Tom’s River

Active Ingredient

Ethyl Alcohol

Purpose

Kills germs,bacteria & odors

Uses

To decrease bacteria on skin

Warnings

● For external use only
● Flammable. Keep away from fire or flame
● Do not use product near or in eyes
● If swallowed, get medical help promptly
● Stop use, ask a doctor if irritation occurs
● Keep out of reach of children

Directions

- Spray directly on hands and rub thoroughly. For children under 6, use adult supervision.
- Not recommended for infants.

Inactive ingredients

Purified Water, Vegetable Glycerin, Lemon Essential Oil, Bergamot Essential Oil, Aloe Vera Gel.